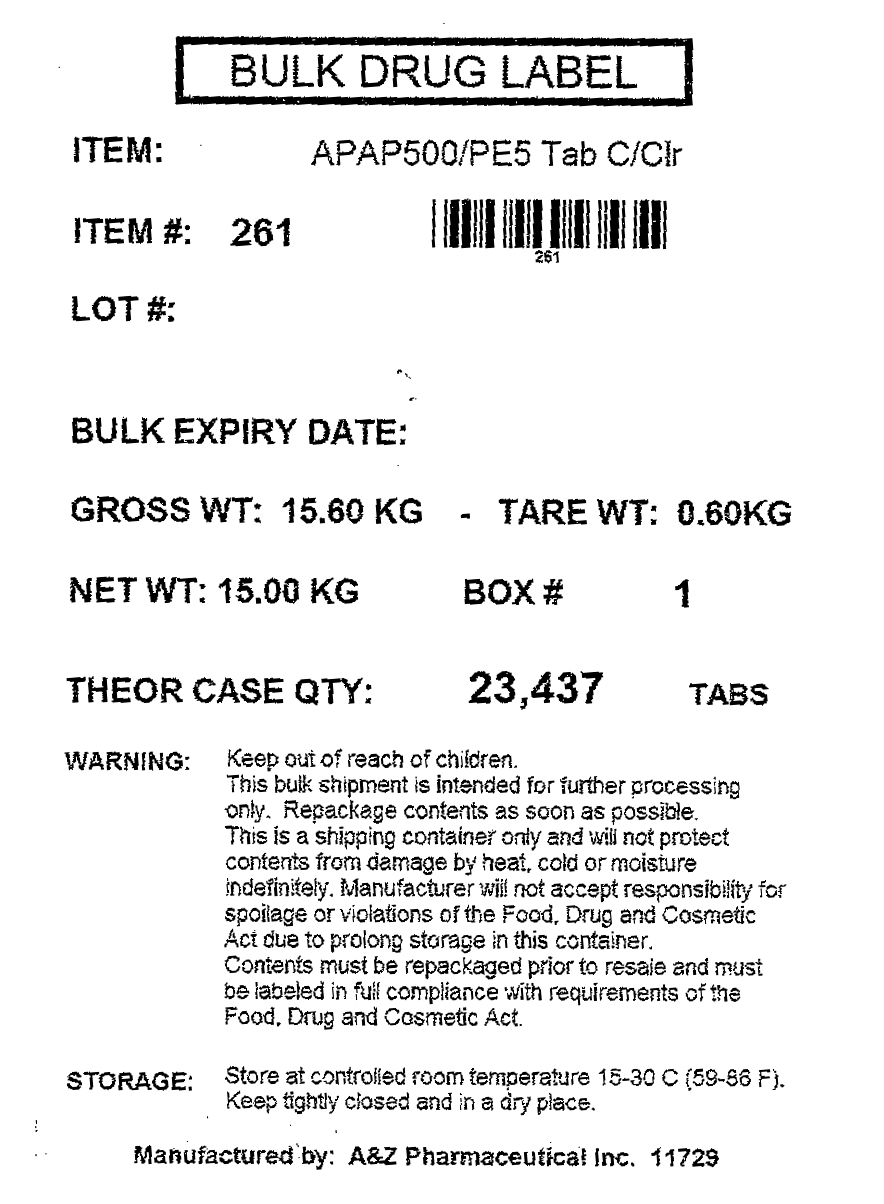 DRUG LABEL: Acetaminophen Phenylephrine HCl
NDC: 69168-261 | Form: TABLET
Manufacturer: Allegiant Health
Category: otc | Type: HUMAN OTC DRUG LABEL
Date: 20140916

ACTIVE INGREDIENTS: ACETAMINOPHEN 500 mg/1 1; PHENYLEPHRINE HYDROCHLORIDE 5 mg/1 1
INACTIVE INGREDIENTS: STARCH, CORN; CROSPOVIDONE; HYPROMELLOSES; CELLULOSE, MICROCRYSTALLINE; POLYETHYLENE GLYCOLS; POVIDONES; STEARIC ACID

Drug Facts

Active ingredient

Acetaminophen 500 mg
Phenylephrine HCl 5 mg

Purpose

Pain reliever
Nasal decongestant

Uses

temporarily relieves nasal and sinus congestion temporarily relieves minor aches and pains, headaches

Warnings

Liver warning: This product contains acetaminophen. Severe liver damage may occur if you take more than 8 tablets in 24 hours, which is the maximum daily amount with other drugs containing acetaminophen 3 or more alcoholic drinks every day while using this product

Do Not Use

if you are now taking a prescription monoamine oxidase inhibitor (MAOI) (certain drugs for depression, psychiatric, or emotional conditions, or Parkinson’s disease), or for 2 weeks after stopping the MAOI drug. If you do not know if your prescription drug contains an MAOI, ask a doctor or pharmacist before taking this product. with any other drug containing acetaminophen (prescription or nonprescription). If you are not sure whether a drug contains acetaminophen, ask a doctor or pharmacist

Ask Doctor before use if you have

liver disease heart disease high blood pressure thyroid disease diabetes trouble urinating due to an enlarged prostate gland

Ask Doctor/Pharmacist before use if you

are taking the blood thinning drug warfarin

When Using

do not use more than directed

Stop use and ask a doctor if

redness or swelling is presentnew symptoms occur you get nervous, dizzy, or sleepless pain gets worse or lasts for more than 7 days ■ fever gets worse or lasts for more than 3 daysYou may report side effects to 800-952-0050

If pregnant or Breast Feeding

ask a health professional before use

Keep Out of Reach of Children

In case of accidental overdose, contact a doctor or Poison Control Center immediately. Prompt medical attention is critical for adults as well as for children even if you do not notice any signs or symptoms

Directions

Adults and children 12 years of age and older: take 2 tablets every 4-6 hours Do not take more than 8 tablets in 24 hours Do not use in children under 12 years of age. This will provide more than the recommended dose (overdose) and could cause serious health problems

Other information

store at room temperature in a dry place do not use if blister package is torn

Inactive Ingredients

corn starch, crospovidone, hydroxypropyl methylcellulose, microcrystalline cellulose, polyethylene glycol, povidone, pregelatinized starch, stearic acid